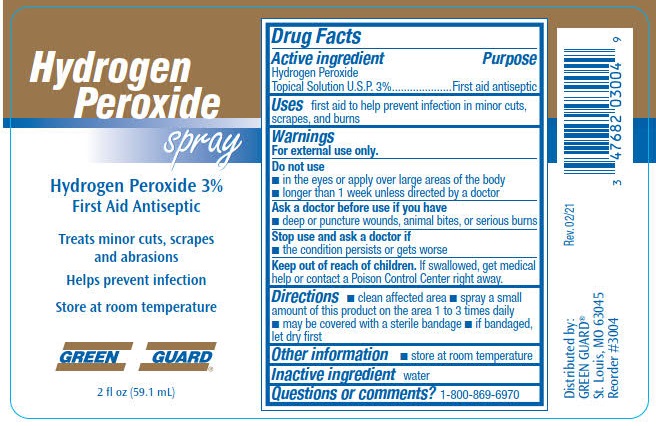 DRUG LABEL: Green Guard Hydrogen Peroxide
NDC: 47682-324 | Form: SPRAY
Manufacturer: Unifirst First Aid Corporation
Category: otc | Type: HUMAN OTC DRUG LABEL
Date: 20240117

ACTIVE INGREDIENTS: HYDROGEN PEROXIDE 30 mL/1 L
INACTIVE INGREDIENTS: WATER

Green Guard Hydrogen Peroxide Spray

Drug Facts

Active ingredient

Hydrogen Peroxide Topical Solution U.S.P. 3%

Purpose

First aid antiseptic

Uses

first aid to help prevent infection in minor cuts, scrapes, and burns

Warnings

Do not use

- in the eyes or apply over large areas of the body
- longer than 1 week unless directed by a doctor

Ask a doctor before use if you have

- deep or puncture wounds, animal bites, or serious burns

Stop use and ask a doctor if

- the condition persists or gets worse

Keep out of reach of children.

If swallowed, get medical help or contact a Poison Control Center right away.

Directions

- clean affected area
- spray a small amount of this product on the area 1 to 3 times daily
- may be covered with a sterile bandage
- if bandaged, let dry first

Other information

- store at room temperature

Inactive ingredient water

Questions or comments? 1-800-869-6970

PACKAGE LABEL

Hydrogen Peroxide spray

Hydrogen Peroxide 3%

First Aid Antiseptic

Treats minor cuts, scrapes and abrasions

Helps prevent infection

Store at room temperature

Green Guard®

2 fl oz (59.1 mL)